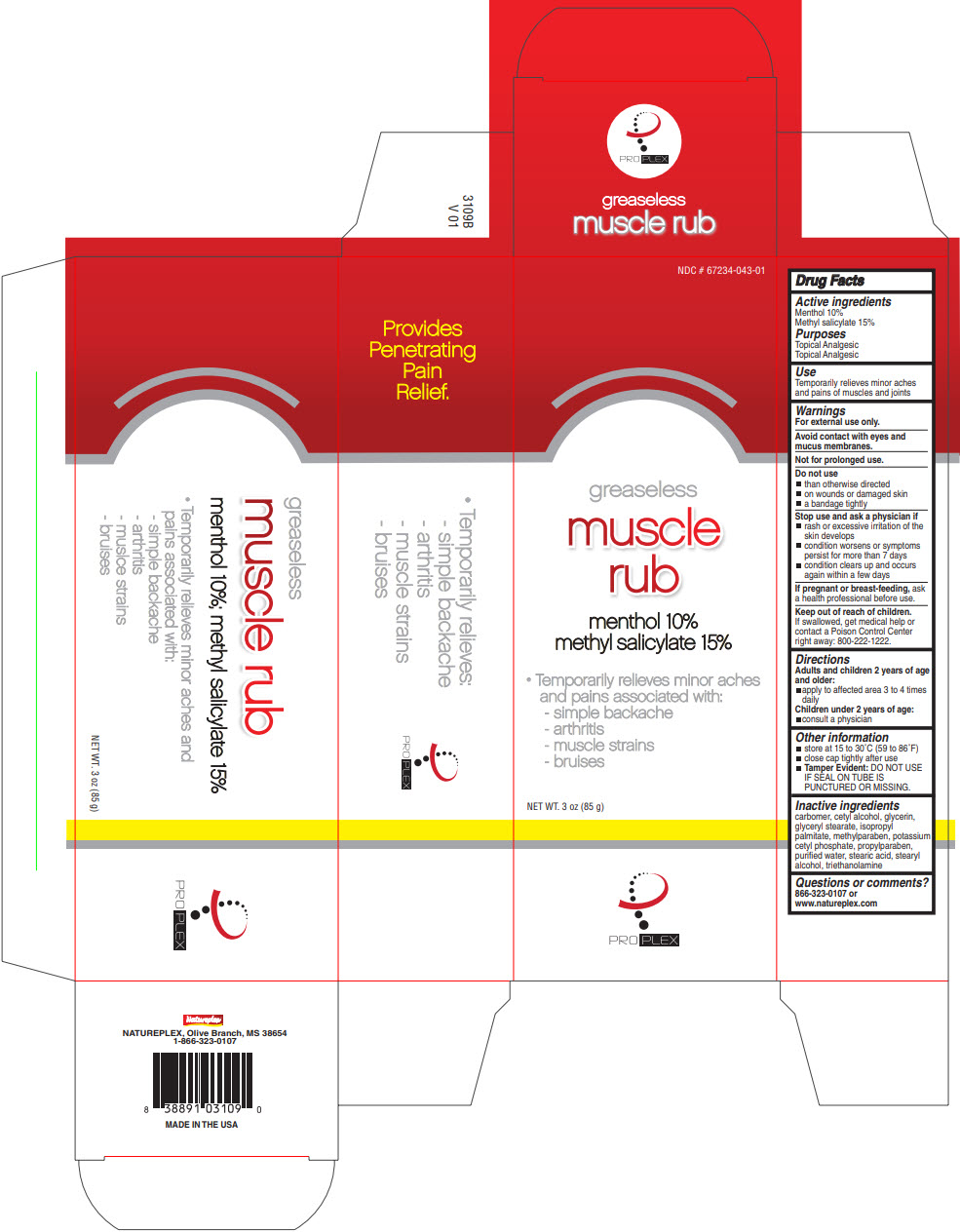 DRUG LABEL: PROPLEX GREASELESS MUSCLE RUB
NDC: 67234-043 | Form: CREAM
Manufacturer: Natureplex LLC
Category: otc | Type: HUMAN OTC DRUG LABEL
Date: 20210112

ACTIVE INGREDIENTS: MENTHOL, UNSPECIFIED FORM 10 mg/1 g; METHYL SALICYLATE 15 mg/1 g
INACTIVE INGREDIENTS: CARBOMER COPOLYMER TYPE A (ALLYL PENTAERYTHRITOL CROSSLINKED); CETYL ALCOHOL; GLYCERIN; GLYCERYL MONOSTEARATE; ISOPROPYL PALMITATE; METHYLPARABEN; POTASSIUM; CETYL PHOSPHATE; PROPYLPARABEN; WATER; STEARIC ACID; STEARYL ALCOHOL; TROLAMINE

PROPLEX GREASELESS MUSCLE RUB

Drug Facts

Active ingredients

Menthol 10%
Methyl salicylate 15%

Purposes

Topical Analgesic
Topical Analgesic

Use

Temporarily relieves minor aches and pains of muscles and joints

Warnings

For external use only.

Avoid contact with eyes and mucus membranes.

Not for prolonged use.

Do not use

- than otherwise directed
- on wounds or damaged skin
- a bandage tightly

Stop use and ask a physician if

- rash or excessive irritation of the skin develops
- condition worsens or symptoms persist for more than 7 days
- condition clears up and occurs again within a few days

PREGNANCY OR BREAST FEEDING

If pregnant or breast-feeding, ask a health professional before use.

Keep out of reach of children.

If swallowed, get medical help or contact a Poison Control Center right away: 800-222-1222.

Directions

Adults and children 2 years of age and older:

- apply to affected area 3 to 4 times daily

Children under 2 years of age:

- consult a physician

Other information

- store at 15 to 30°C (59 to 86°F)
- close cap tightly after use
- Tamper Evident: DO NOT USE IF SEAL ON TUBE IS PUNCTURED OR MISSING.

Inactive ingredients

carbomer, cetyl alcohol, glycerin, glyceryl stearate, isopropyl palmitate, methylparaben, potassium cetyl phosphate, propylparaben, purified water, stearic acid, stearyl alcohol, triethanolamine

Questions or comments?

866-323-0107 or www.natureplex.com

PRINCIPAL DISPLAY PANEL - 85 g Tube Carton

NDC # 67234-043-01

greaseless

muscle
rub

menthol 10%
methyl salicylate 15%

- Temporarily relieves minor aches
  and pains associated with:
  - simple backache
  - arthritis
  - muscle strains
  - bruises

NET WT. 3 oz (85 g)

PRO PLEX